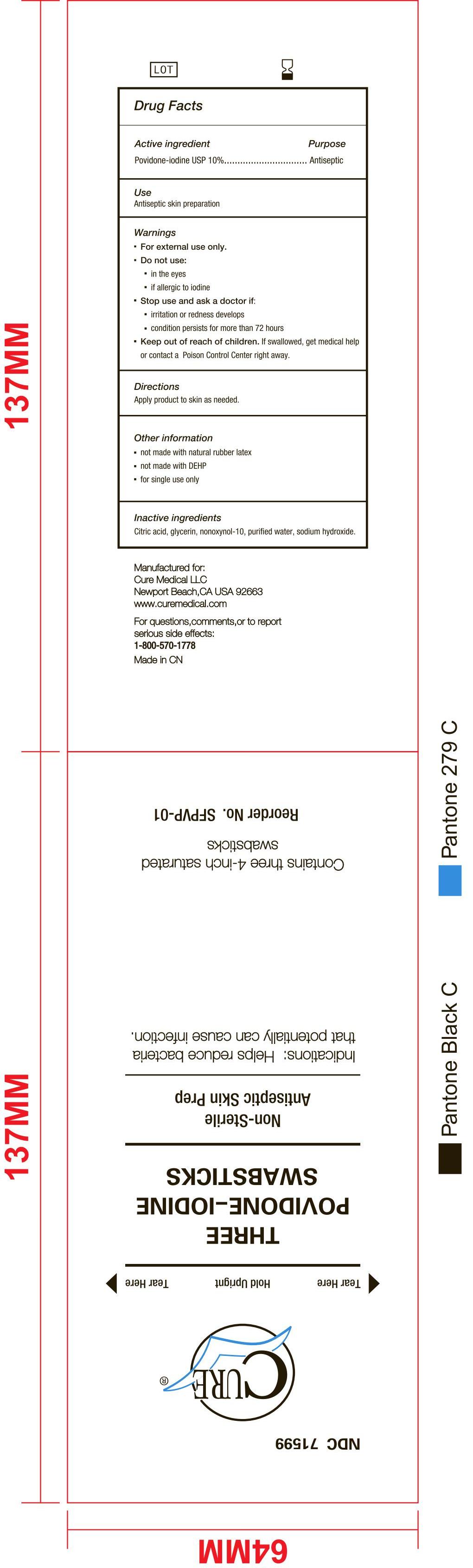 DRUG LABEL: Cure Povidone Iodine Swabsticks
NDC: 71599-002 | Form: SWAB
Manufacturer: Cure Medical LLC
Category: otc | Type: HUMAN OTC DRUG LABEL
Date: 20180805

ACTIVE INGREDIENTS: POVIDONE-IODINE 0.2 g/1 1
INACTIVE INGREDIENTS: WATER; CITRIC ACID MONOHYDRATE; SODIUM HYDROXIDE; GLYCERIN; NONOXYNOL-10

Active Ingredient: Povidone-Iodine USP (10%)

Purpose: Antiseptic

INDICATIONS AND USAGE

Use: Antiseptic skin preparation

Warnings:

Do not use

- if allergic to iodine
- in the eyes

For external use only

Keep out of reach of children. In case of accidental ingestion, seek professional assistance or consult a poison control center immediately

Stop use and ask a doctor if

- irritation or redness develops
- condition persists for more than 72 hours

DOSAGE AND ADMINISTRATION

Apply product to skin as need

Other information

- Not made with nature rubber latex
- Not made with DEHP
- For single use only

Inactive Ingredient

Citric Acid, Glycerin, Nonoxyol-10, Sodium Hydroxide, Water